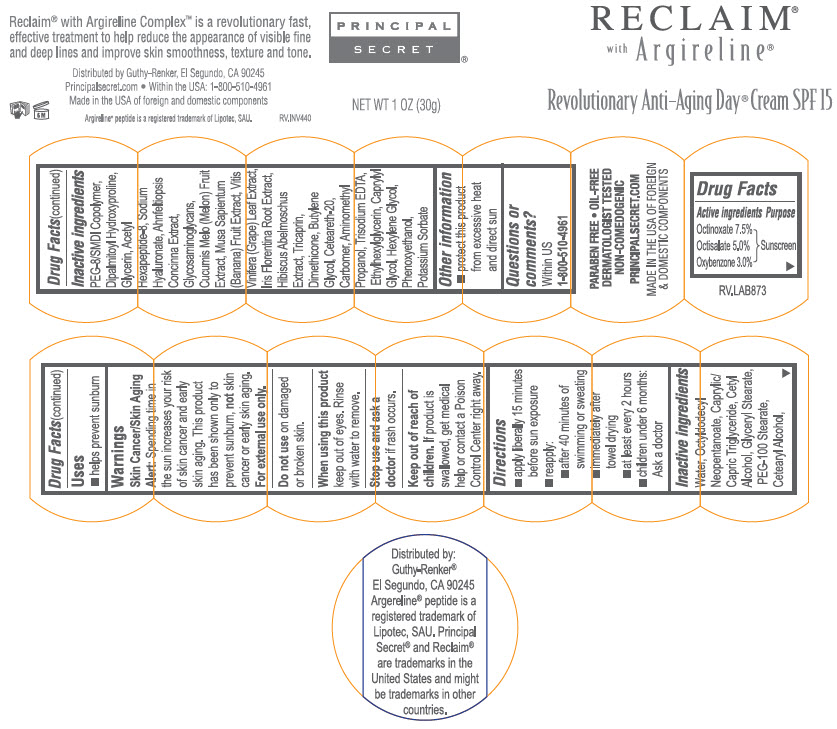 DRUG LABEL: Reclaim Revolutionary Anti-Aging Day SPF15
NDC: 70605-042 | Form: CREAM
Manufacturer: Guthy-Renker LLC
Category: otc | Type: HUMAN OTC DRUG LABEL
Date: 20251223

ACTIVE INGREDIENTS: Octinoxate 7.5 g/100 g; Octisalate 5 g/100 g; Oxybenzone 3 g/100 g
INACTIVE INGREDIENTS: OCTYLDODECYL NEOPENTANOATE; MEDIUM-CHAIN TRIGLYCERIDES; CETYL ALCOHOL; GLYCERYL MONOSTEARATE; PEG-100 STEARATE; CETOSTEARYL ALCOHOL; DIPALMITOYL HYDROXYPROLINE; PEG-8/SMDI COPOLYMER; GLYCERIN; ACETYL HEXAPEPTIDE-8 AMIDE; HYALURONATE SODIUM; AHNFELTIOPSIS CONCINNA; MUSKMELON; BANANA; VITIS VINIFERA LEAF; IRIS X GERMANICA NOTHOVAR. FLORENTINA ROOT; TRICAPRIN; DIMETHICONE; BUTYLENE GLYCOL; POLYOXYL 20 CETOSTEARYL ETHER; TROLAMINE; EDETATE TRISODIUM; ETHYLHEXYLGLYCERIN; CAPRYLYL GLYCOL; HEXYLENE GLYCOL; POTASSIUM SORBATE; PHENOXYETHANOL

Reclaim® Revolutionary Anti-Aging Day® Cream SPF15

Drug Fact Label

Active ingredient

Octinoxate 7.5%
Octisalate 5.0%
Oxybenzone 3.0%

Purpose

Sunscreen

Uses

- Helps prevent sunburn

Warnings

- Skin Cancer/Skin Aging Alert: Spending time in the sun increases your risk of skin cancer and early skin aging. This product has been shown only to prevent sunburn not skin cancer or early skin aging.

For external use only.

- Do not use on damaged or broken skin.

- When using this product keep out of eyes. Rinse with water to remove.

Stop use and ask a doctor if rash occurs

Keep out of reach of children

- If product is swallowed, get medical help or contact a Poison Control Center right away.

Directions

- Apply liberally 15 minutes before sun exposure.
- reapply:
- after 40 minutes of swimming or sweating
- immediately after towel drying
- at least 2 hours
- Children under 6 months: Ask a doctor.

Inactive ingredients

Water, Octyldodecyl Neopentanoate, Caprylic/Capric Triglyceride, Cetyl Alcohol, Glyceryl Stearate, PEG-100 Stearate, Cetearyl Alcohol, PEG-8/SMDI Copolymer, Dipalmitoyl Hydroxyproline, Glycerin, Acetyl Hexapeptide-8, Sodium Hyaluronate, Ahnfeltia Concinna Extract, Glycosaminoglycans, Cucumis Melo (Melon) Fruit Extract, Musa Sapientum (Banana) Fruit Extract, Vitis Vinifera (Grape) Leaf Extract, Iris Florentina Extract, Hibiscus Abelmoschuus Extract, Tricaprin, Dimethicone, Butylene Glycol, Cetereath-20, Carbomer, Aminomethyl Propanol, Trisodium EDTA, Ethylhexylglycerin, Caprylyl Glycol, Hexylene Glycol, Phenoxyethanol, Potassium Sorbate.

Other information

- Protect this product from excessive heat and direct sun.

Questions or comments?

Within US 1-800-510-4961

Distributed by:
Guthy-Renker®
El Segundo, CA 90245

PRINCIPAL DISPLAY PANEL - 30g Jar Label

RECLAIM®
with Argireline®

Revolutionary Anti-Aging Day® Cream SPF 15